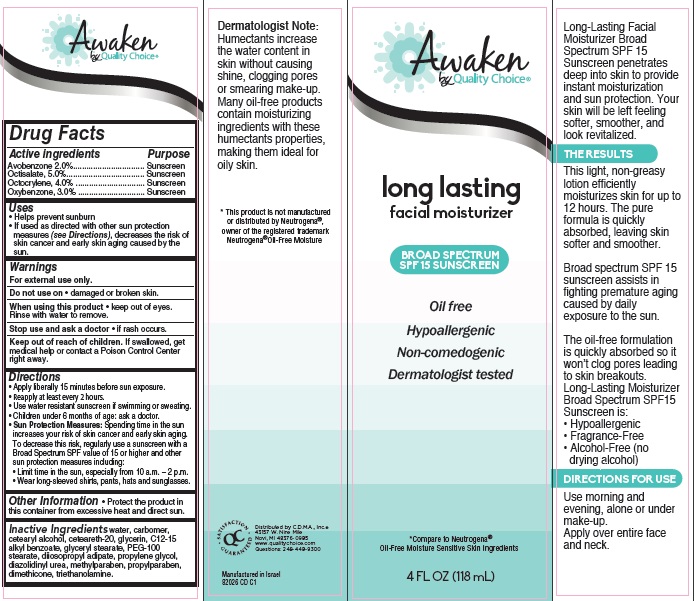 DRUG LABEL: Awaken by Quality Choice Long-Lasting Oil-Free Moisturizer Broad Spectrum SPF 15
NDC: 63868-255 | Form: CREAM
Manufacturer: Chain Drug Marketing Association
Category: otc | Type: HUMAN OTC DRUG LABEL
Date: 20140930

ACTIVE INGREDIENTS: AVOBENZONE 2 g/100 g; OCTISALATE 5 g/100 g; OCTOCRYLENE 4 g/100 g; OXYBENZONE 3 g/100 g
INACTIVE INGREDIENTS: WATER; CETOSTEARYL ALCOHOL; POLYOXYL 20 CETOSTEARYL ETHER; GLYCERIN; ALKYL (C12-15) BENZOATE; GLYCERYL MONOSTEARATE; PEG-100 STEARATE; DIISOPROPYL ADIPATE; PROPYLENE GLYCOL; DIAZOLIDINYL UREA; METHYLPARABEN; PROPYLPARABEN; DIMETHICONE; TROLAMINE

Awaken by Quality Choice® Long Lasting Facial Moisturizer Broad Spectrum SPF 15 Sunscreen

Active ingredient

Avobenzone 2.0%

Octisalate, 5.0%

Octocrylene, 4.0%

Oxybenzone, 3.0%

Purpose

Sunscreen

Uses

- helps prevent sunburn
- If used as directed with other sun protection measures (see Directions), decreases the risk of skin cancer and early skin aging caused by the sun.

Warnings

For external use only.

Do not use on

- damaged or broken skin.

When using this product

- keep out of eyes. Rinse with water to remove.

Stop use and ask a doctor

- if rash occurs.

Keep Out of Reach of Children.

If swallowed, get medical help or contact a Poison Control Center right away.

Directions

- Apply liberally 15 minutes before sun exposure.
- Reapply at least every 2 hours.
- Use water resistant sunscreen if swimming or sweating.
- Children under 6 months of age: ask a doctor.
- Sun Protection Measures: Spending time in the sun increases your risk of skin cancer and early skin aging. To decrease this risk, regularly use a sunscreen with a Broad Spectrum SPF value of 15 or higher and other sun protection measures including:
  1. Limit time in the sun, especially from 10 a.m. - 2 p.m.
  2. Wear long-sleeved shirts, pants, hats and sunglasses.

Other Information

- Protect the product in this container from excessive heat and direct sun.

Inactive Ingredients

water, carbomer, cetearyl alcohol, ceteareth-20, glycerin, C12-15 alkyl benzoate, glyceryl stearate, PEG-100 stearate, diiosopropyl adipate, propylene glycol, diazolidinyl urea, methylparaben, propylparaben, dimethicone, triethanolamine.

Package/Label Principal Display Panel

Awaken
by Quality Choice®

long lasting
facial moisturizer

BROAD SPECTRUM
SPF 15 SUNSCREEN

Oil free

Hypoallergenic

Non-comedogenic

Dermatologist tested

*Compare to Neutrogena®
Oil-Free Moisture Sensitive Skin Ingredients

4 FL OZ (118 mL)

Long-Lasting Facial Moisturizer Broad Spectrum SPF 15 Sunscreen penetrates deep into skin to provide instant moisturization and sun protection. Your skin will be left feeling softer, smoother, and look revitalized.

THE RESULTS

This light, non-greasy lotion efficiently moisturizes skin for up to 12 hours. The pure formula is quickly absorbed, leaving skin softer and smoother.

Broad spectrum SPF 15 sunscreen assists in fighting premature aging caused by daily exposure to the sun.

The oil-free formulation is quickly absorbed so it won’t clog pores leading to skin breakouts.
Long-Lasting Moisturizer Broad Spectrum SPF15 Sunscreen is:

- Hypoallergenic
- Fragrance-Free
- Alcohol-Free (no drying alcohol)

DIRECTIONS FOR USE

Use morning and evening, alone or under make-up.
Apply over entire face and neck.

Dermatologist Note:
Humectants increase the water content in skin without causing shine, clogging pores or smearing make-up. Many oil-free products contain moisturizing ingredients with these humectants properties, making them ideal for oily skin.

*This product is not manufactured or distributed by Neutrogena®, owner of the registered trademark Neutrogena® Oil-Free Moisture

SATISFACTION GUARANTEED

Distributed by C.D.M.A., Inc.©
43157 W. Nine Mile
Novi, MI 48376-0995
www.qualitychoice.com
Questions: 248-449-9300

Manufactured in Israel
82026 CD C1

Carton Label